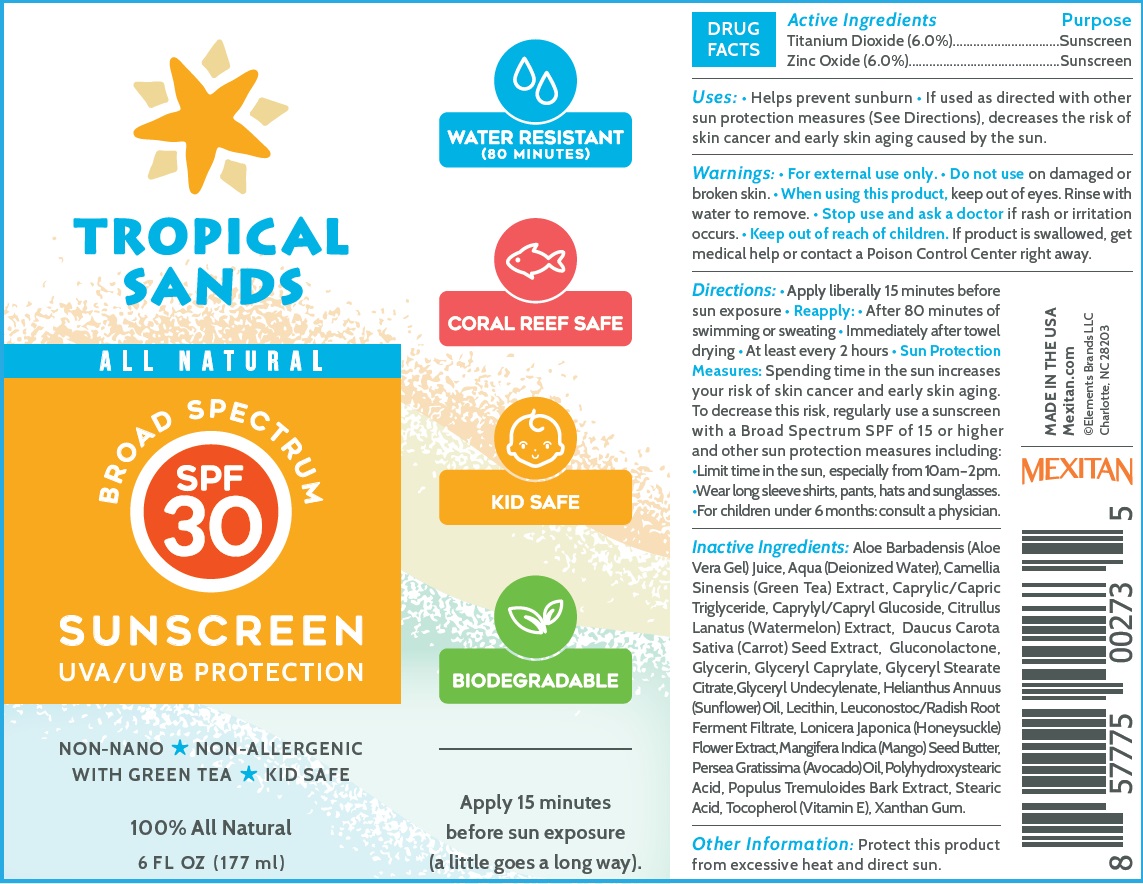 DRUG LABEL: Tropical Sands SPF-30 Broad Spectrum Sunscreen
NDC: 71221-795 | Form: CREAM
Manufacturer: Elements Brands, Inc.
Category: otc | Type: HUMAN OTC DRUG LABEL
Date: 20231111

ACTIVE INGREDIENTS: TITANIUM DIOXIDE 60 mg/1 mL; ZINC OXIDE 60 mg/1 mL
INACTIVE INGREDIENTS: ALOE VERA LEAF; WATER; GREEN TEA LEAF; MEDIUM-CHAIN TRIGLYCERIDES; CAPRYLYL/CAPRYL OLIGOGLUCOSIDE; WATERMELON; DAUCUS CAROTA SUBSP. SATIVUS SEED; GLUCONOLACTONE; GLYCERIN; GLYCERYL MONOCAPRYLATE; GLYCERYL STEARATE CITRATE; GLYCERYL 1-UNDECYLENATE; HELIANTHUS ANNUUS FLOWERING TOP; LEUCONOSTOC/RADISH ROOT FERMENT FILTRATE; LONICERA JAPONICA FLOWER; MANGIFERA INDICA SEED BUTTER; AVOCADO OIL; POPULUS TREMULOIDES BARK; STEARIC ACID; TOCOPHEROL; XANTHAN GUM

Tropical Sands SPF-30 Broad Spectrum Sunscreen

Active Ingredients

Titanium Dioxide (6.0%)

Zinc Oxide (6.0%)

Purpose

Sunscreen

Uses:

• Helps prevent sunburn • If used as directed with other sun protection measures (See Directions), decreases the risk of skin cancer and early skin aging caused by the sun.

Warnings:

• For external use only.

Do not use

on damaged or broken skin.

When using this product

keep out of eyes. Rinse with water to remove.

Stop use and ask a doctor

if rash or irritation occurs.

Keep out of reach of children.

If product is swallowed, get medical help or contact a Poison Control Center right away.

Directions:

• Apply liberally 15 minutes before sun exposure • Reapply: • After 80 minutes of swimming or sweating • Immediately after towel drying • At least every 2 hours • Spending time in the sun increases your risk of skin cancer and early skin aging. To decrease this risk, regularly use a sunscreen with a Broad Spectrum SPF of 15 or higher and other sun protection measures including: •Limit time in the sun, especially from 10 am – 2 pm. •Wear long sleeve shirts, pants, hats and sunglasses. •For children under 6 months: consult a physician. Sun Protection Measures:

Inactive Ingredients:

Aloe Barbadensis (Aloe Vera Gel) Juice, Aqua (Deionized Water), Camellia Sinensis (Green Tea) Extract, Caprylic/Capric Triglyceride, Caprylyl/Capryl Glucoside, Citrullus Lanatus (Watermelon) Extract, Daucus Carota Sativa (Carrot) Seed Extract, Gluconolactone, Glycerin, Glyceryl Caprylate, Glyceryl Stearate Citrate,Glyceryl Undecylenate, Helianthus Annuus (Sunflower) Oil, Lecithin, Leuconostoc/Radish Root Ferment Filtrate, Lonicera Japonica (Honeysuckle) Flower Extract, Mangifera Indica (Mango) Seed Butter, Persea Gratissima (Avocado) Oil, Polyhydroxystearic Acid, Populus Tremuloides Bark Extract, Stearic Acid, Tocopherol (Vitamin E), Xanthan Gum.

Other Information:

Protect this product from excessive heat and direct sun.